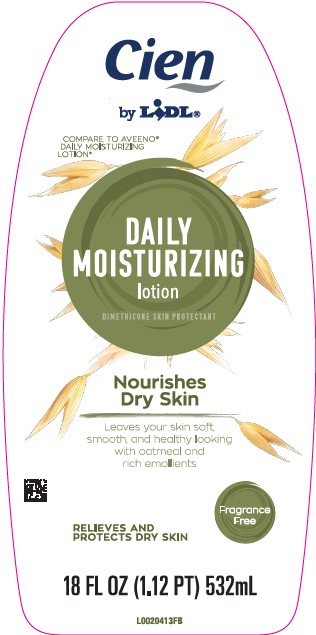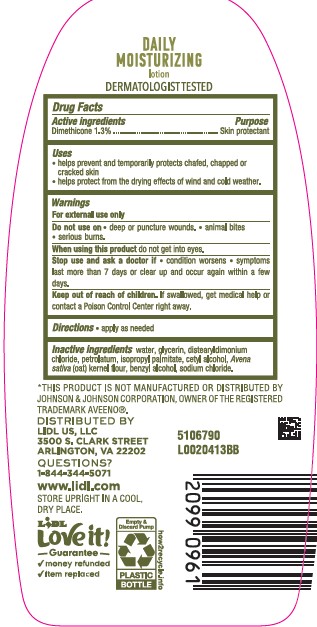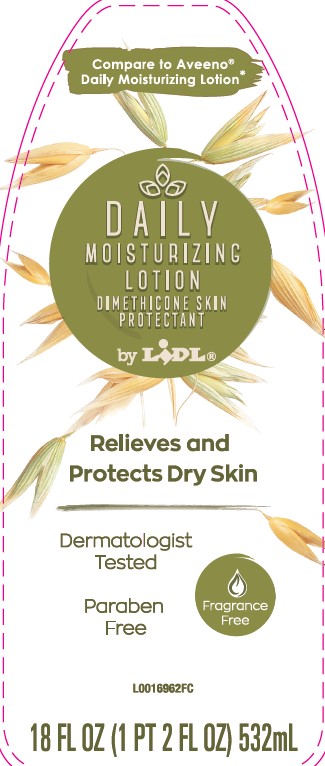 DRUG LABEL: Daily Moisturizing
NDC: 71141-619 | Form: LOTION
Manufacturer: Lidl US, LLC
Category: otc | Type: HUMAN OTC DRUG LABEL
Date: 20260204

ACTIVE INGREDIENTS: DIMETHICONE 1.3 kg/100 mL
INACTIVE INGREDIENTS: WATER; GLYCERIN; DISTEARYLDIMONIUM CHLORIDE; PETROLATUM; ISOPROPYL PALMITATE; CETYL ALCOHOL; OATMEAL; BENZYL ALCOHOL; SODIUM CHLORIDE

Lidl 619.003/619AC rev 2
Daily Moisturizing Lotion

Claims

DAILY MOISTURIZING

lotion

DERMATOLOGIST TESTED

Active Ingredient

Dimethicone 1.3%

Purpose

Skin protectant

Uses

- helps prevent and temporarily protects chafed, chapped or cracked skin
- helps protect from the drying effects of wind and cold weather

Warnings

For external use only

Do Not Use

- on deep or puncture wounds
- animal bites
- serious burns

When using this product

do not get into eyes

Stop Use and ask a doctor if

- condition worsens
- symptoms last more than 7 days or clear up and occur again within a few days

Keep out of reach of children.

If swallowed, get medical help or contact a Poison Control Center right away.

Directions

- apply as needed

Inactive ingredients

water, glycerin, distearyldimonium chloride, petrolatum, isopropyl palmitate, cetyl alcohol, Avena sativa (oat) kernel flour, benzyl alcohol, sodium chloride

Disclaimer

*THIS PRODUCT IS NOT MANUFACTURED OR DISTRIBUTED BY JOHNSON & JOHNSON CORPOARATION, OWNER OF THE REGISTERED TRADEMARK AVEENO®.

ADVERSE REACTION

DISTRIBUTED BY

LIDL US, LLC

3500 S. Clark Street

Arlington, VA 22202

QUESTIONS?

1-844-344-5071

www.lidl.com

STORE UPRIGHT IN A COOL, DRY PLACE.

LiDL

love it!

Guarantee

- money refunded
- item replaced

Empty & Discard Pump

PLASTIC BOTTLE

how2recycle.info

Principal display panel

Compare to Aveeno

Daily Moisturizing Lotion

DAILY

MOISTURIZING

LOTION

DIMETHICONE SKIN

PROTECTANT

by LIDl

Relieves and Protects Dry Skin

Dermatologist Tested

Fragrance Free

Paraben Free

18 FL OZ (1 PT 2 FL OZ) 532 mL

Principal display panel

Cien

by LiDL®

COMPARE TO AVEENO®DAILY MOISTURIZING LOTION*

DAILY MOISTURIZING lotion

DIMETHICONE SKIN PROTECTANT

Nourishes Dry Skin

Leaves your skin soft, smooth, and healthy looking with oatmeal and rich emoilents

Fragrance Free

RELIEVES AND PROTECTS DRY SKIN

18 FL OZ (1.12 PT) 532 mL